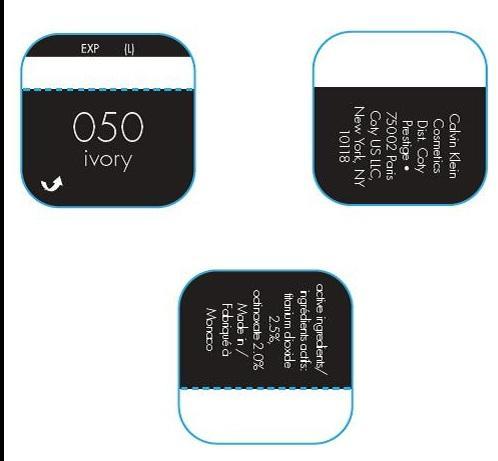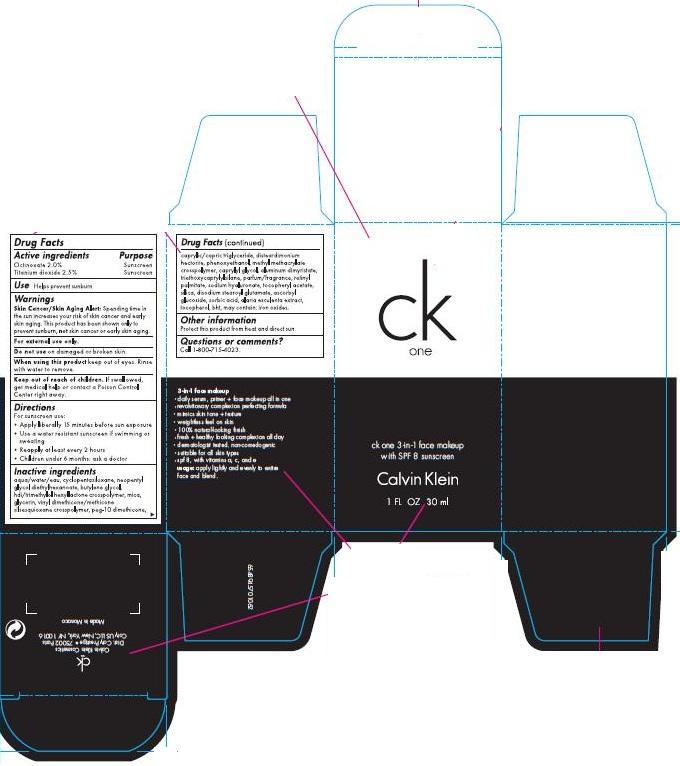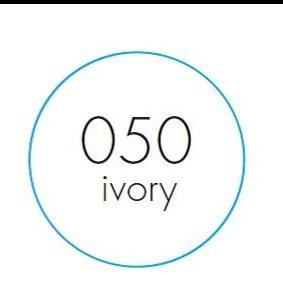 DRUG LABEL: ck one 3-in-1 face makeup
NDC: 66184-401 | Form: LIQUID
Manufacturer: Coty US LLC
Category: otc | Type: HUMAN OTC DRUG LABEL
Date: 20131212

ACTIVE INGREDIENTS: Titanium Dioxide 0.302 g/30 mL; Octinoxate  0.606 g/30 mL
INACTIVE INGREDIENTS: Water; CYCLOMETHICONE 5 ; Neopentyl Glycol ; Butylene Glycol ; PEG-10 DIMETHICONE (600 CST); Tricaprin ; Phenoxyethanol ; Methyl Methacrylate ; Caprylyl Glycol ; Aluminum Dimyristate ; Triethoxycaprylylsilane; Vitamin A Palmitate ; Hyaluronate Sodium ; Alpha-Tocopherol Acetate ; Silicon Dioxide; Disodium Stearoyl Glutamate ; Sorbic Acid; Alaria Esculenta ; Tocopherol ; BUTYLATED HYDROXYTOLUENE 

Drug Facts

ACTIVE INGREDIENT

Octinoxate 2.0%

Titanium Dioxide 2.5%

PURPOSE

Sunscreen

Keep out of reach of children. If swallowed, get medical help or contact a Poison Control Center right away.

INDICATIONS AND USAGE

Helps prevent sunburn.

WARNINGS

Skin Cancer/Skin Aging Alert: Spending time in the sun increases your risk of skin cancer and early skin aging. This product has been shown only to prevent sunburn, no skin cancer or early skin aging.

DOSAGE AND ADMINISTRATION

- Apply liberally 15 minutes before sun exposure
- Use a water resistant sunscreen if swimming or sweating
- Reapply at least every 2 hours
- Children under months: ask a doctor

INACTIVE INGREDIENT

aqua/water/eau, cyclopentasiloxane, neopentyl glycol diethylhexanoate, butylene glycol, hdi/trimethylol crosspolymer, mica, glycerin, vinyl dimethicone/methicone silsesquioxane crosspolymer, peg-10 dimethicone, caprylic/capric triglyceride, disteardimonium hectorite, phenoxyethanol, methyl methacrylate crosspolymer, caprylyl glycol, aluminum dimyristate, triethoxycaprylylsilane, parfum/fragrance, retinyl palmitate, sodium hyaluronate, tocopheryl acetate, silica, disodium stearoyl glutamate, ascorbyl glucoside, sorbic acid, alaria esculenta extract, tocopherol, bht, [may contain: iron oxides]